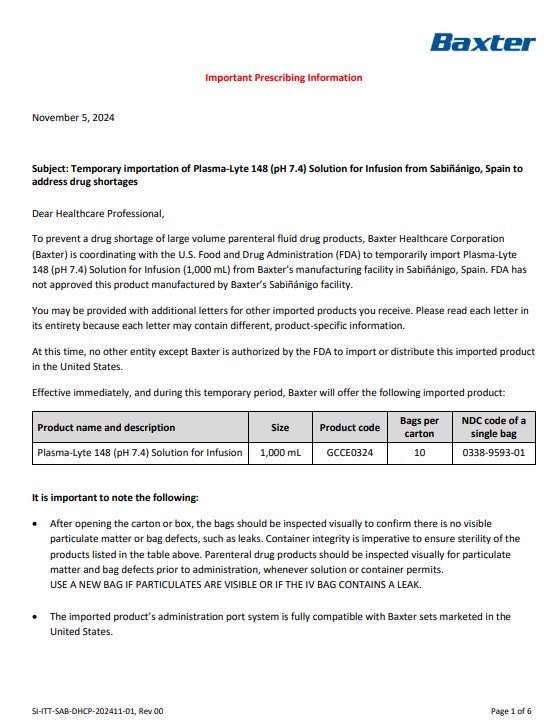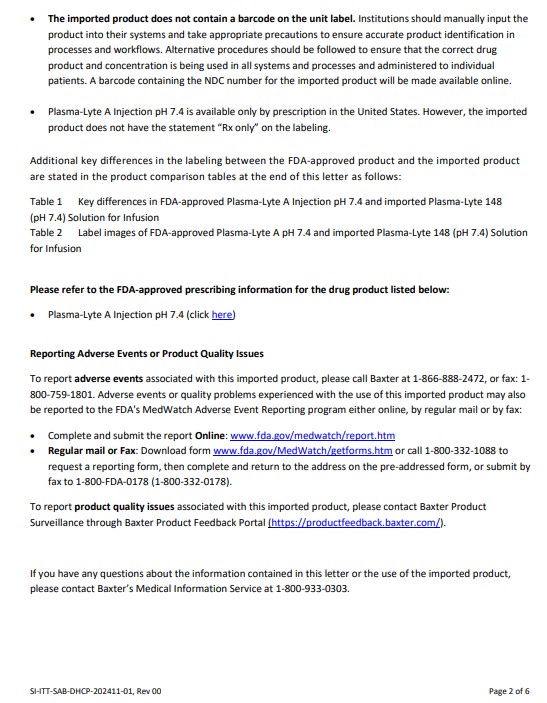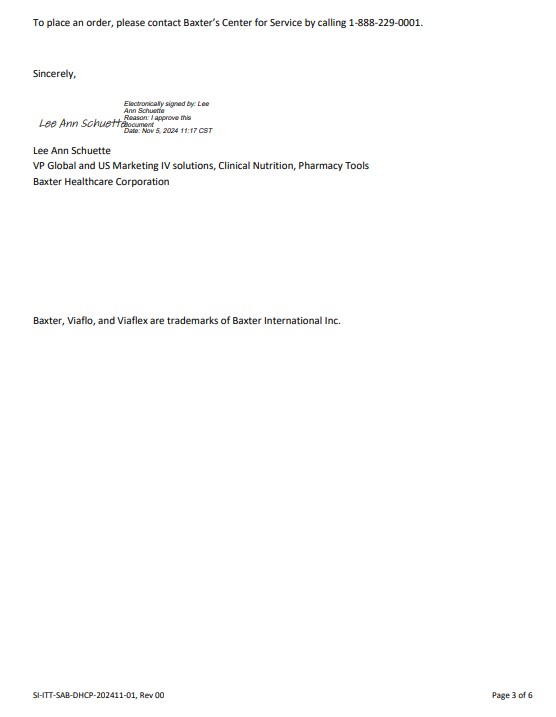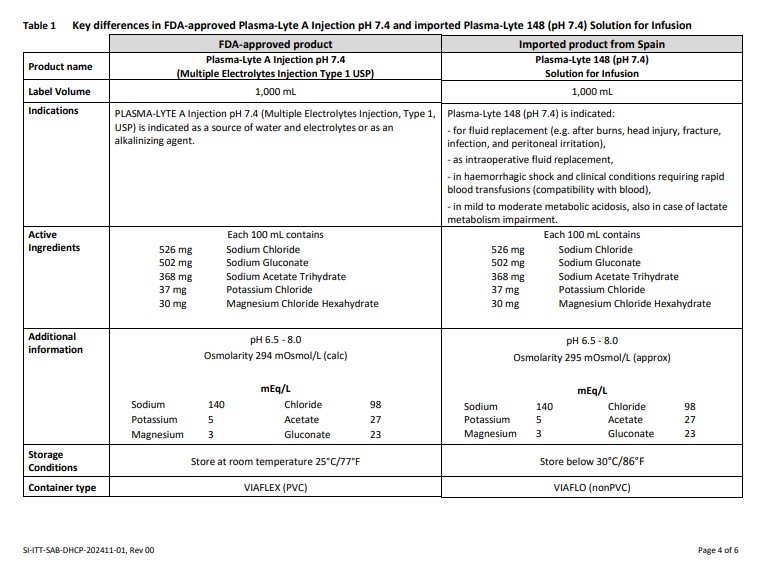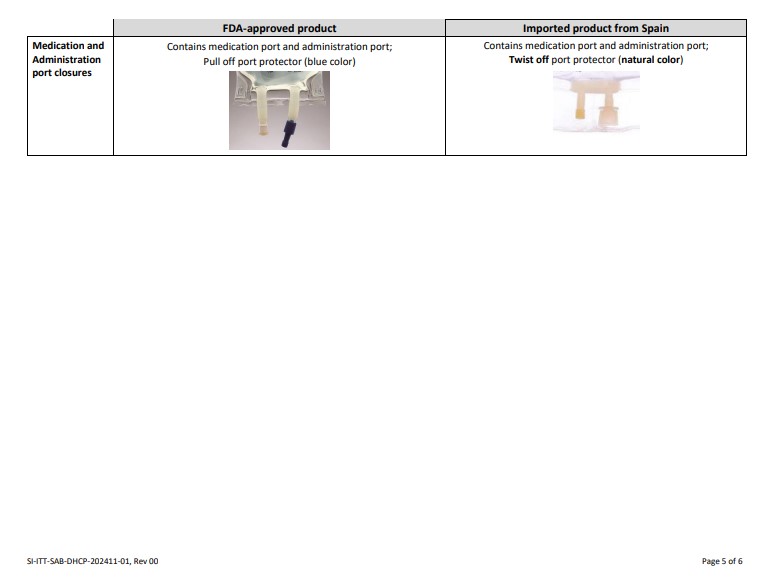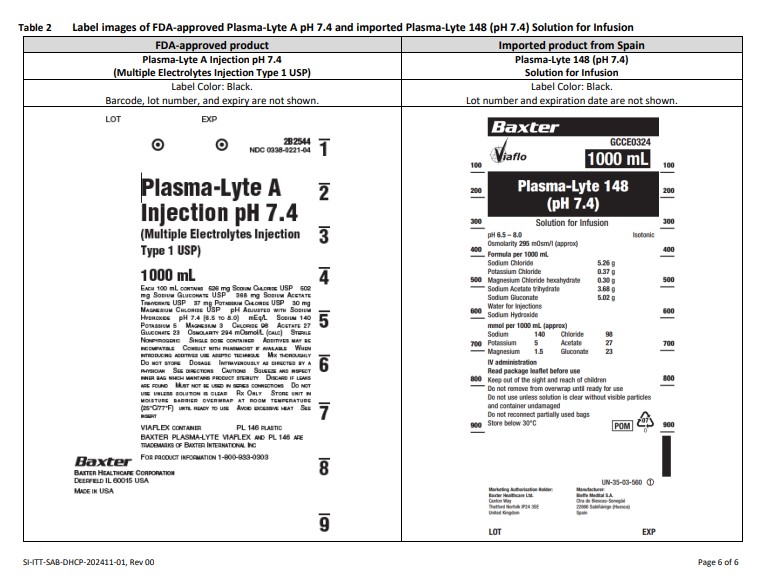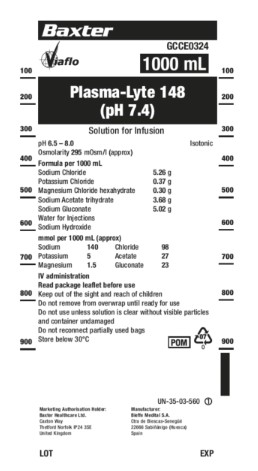 DRUG LABEL: Plasma-Lyte 148 (pH 7.4)
NDC: 0338-9593 | Form: INJECTION, SOLUTION
Manufacturer: Baxter Healthcare Corporation
Category: prescription | Type: HUMAN PRESCRIPTION DRUG LABEL
Date: 20241108

ACTIVE INGREDIENTS: SODIUM CHLORIDE 526 mg/100 mL; SODIUM GLUCONATE 502 mg/100 mL; SODIUM ACETATE 368 mg/100 mL; POTASSIUM CHLORIDE 37 mg/100 mL; MAGNESIUM CHLORIDE 30 mg/100 mL
INACTIVE INGREDIENTS: WATER; SODIUM HYDROXIDE

PLASMA-LYTE 148 (pH 7.4)

Healthcare Professional Letter

Please refer to the FDA-approved prescribing information for the drug product listed below:
• Plasma-Lyte A Injection pH 7.4 (click here)

• Complete and submit the report Online: http://www.fda.gov/medwatch/report.htm
• Regular mail or Fax: Download form http://www.fda.gov/MedWatch/getforms.htm or call 1-800-332-1088 to request a reporting form, then complete and return to the address on the pre-addressed form, or submit by fax to 1-800-FDA-0178 (1-800-332-0178).

To report product quality issues associated with this imported product, please contact Baxter Product Surveillance through Baxter Product Feedback Portal (https://productfeedback.baxter.com/)

PACKAGE/LABEL PRINCIPAL DISPLAY PANEL

Container Label

Baxter

Viaflo

GCCE0324

1000 mL

100

200

300

400

500

600

700

800

900

Plasma-Lyte 148
(pH 7.4)

Solution for Infusion

pH 6.5 – 8.0
Isotonic
Osmolarity 295 m0sm/l (approx)

Formula per 1000ml
Sodium Chloride5.26 g
Potassium Chloride 0.37 g
Magnesium Chloride hexahydrate 0.30 g
Sodium Acetate trihydrate3.68 g
Sodium Gluconate5.02 g
Water for Injections
Sodium Hydroxide

mmol per 100 mL (approx)
Sodium 140 Chloride 98
Potassium 5 Acetate 27
Magnesium 1.5 Gluconate 23

IV administration
Read package leaflet before use
Keep out of the sight and reach of children
Do not remove from overwrap until ready for use
Do not use unless solution is clear without visible particles
and container undamaged
Do not reconnect partially used bags
Store below 30oC

POM
07
0

UN-35-03-560
1

Marketing Authorization Holder:
Baxter Healthcare Ltd.
Caxton Way
Thetford Norfolk IP 24 3SE
United Kingdom

Manufacturer:
Bieffe Medital S.A.

Ctra de Biescas-Senegüé
22666 Sabiñánigo (Huesca)
Spain

LOT

EXP